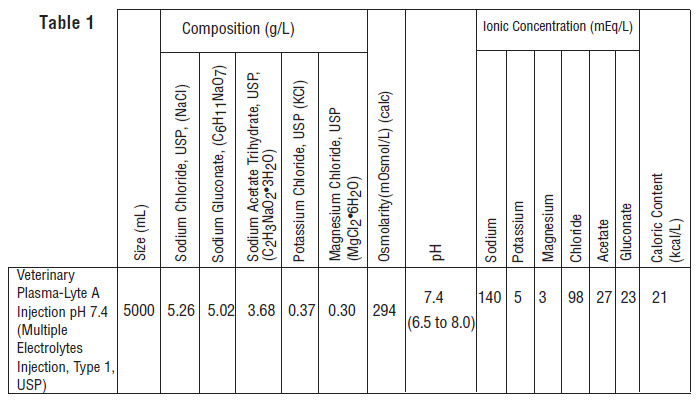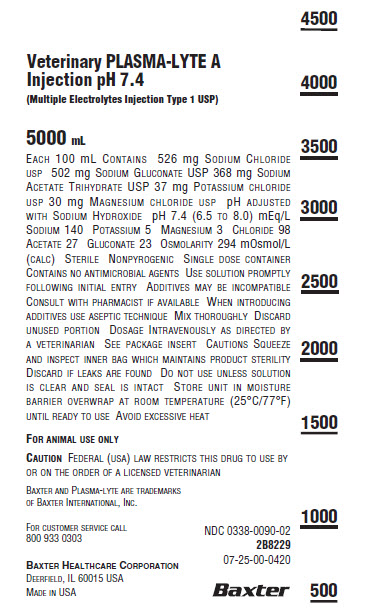 DRUG LABEL: Veterinary PLASMA-LYTE A
NDC: 0338-0090 | Form: INJECTION, SOLUTION
Manufacturer: Baxter Healthcare Corporation
Category: animal | Type: PRESCRIPTION ANIMAL DRUG LABEL
Date: 20200728

ACTIVE INGREDIENTS: SODIUM CHLORIDE 526 mg/100 mL; SODIUM GLUCONATE 502 mg/100 mL; SODIUM ACETATE 368 mg/100 mL; POTASSIUM CHLORIDE 37 mg/100 mL; MAGNESIUM CHLORIDE 30 mg/100 mL
INACTIVE INGREDIENTS: WATER

VETERINARY PLASMA-LYTE A

DESCRIPTION

PLASMA-LYTE A Injection pH 7.4 (Multiple Electrolytes Injection, Type 1, USP) is a sterile, nonpyrogenic isotonic solution in a single dose container for intravenous administration. It contains no antimicrobial agents. Discard unused portion. The pH is adjusted with sodium hydroxide. Composition, osmolarity, pH, ionic concentration and caloric content are shown in Table 1.

PLASMA-LYTE A Injection pH 7.4 (Multiple Electrolytes Injection, Type 1, USP) administered intravenously has value as a source of water,
electrolytes, and calories. Normal physiologic osmolarity range is 280 to 310 mOsmol/L. Administration of substantially hypertonic solutions may cause vein damage.
The plastic container is fabricated from a specially formulated polyvinyl chloride. The amount of water that can permeate from inside the container into the overwrap is insufficient to affect the solution significantly.
Solutions in contact with the plastic container can leach out certain of its chemical components in very small amounts within the expiration period, e.g., di-2-ethylhexyl phthalate (DEHP), up to 5 parts per million. However, the safety of the plastic has been confirmed in tests in animals according to USP biological tests for plastic containers as well as by tissue culture toxicity studies.

CLINICAL PHARMACOLOGY

PLASMA-LYTE A Injection pH 7.4 (Multiple Electrolytes Injection, Type 1, USP) has value as a source of water and electrolytes. It is capable of inducing diuresis depending on the clinical condition of the patient.
PLASMA-LYTE A Injection pH 7.4 (Multiple Electrolytes Injection, Type 1, USP) produces a metabolic alkalinizing effect. Acetate and gluconate ions are metabolized ultimately to carbon dioxide and water, which requires the consumption of hydrogen cations.

INDICATIONS AND USAGE

PLASMA-LYTE A Injection pH 7.4 (Multiple Electrolytes Injection, Type 1, USP) is indicated as a source of water and electrolytes or as an alkalinizing agent.
PLASMA-LYTE A Injection pH 7.4 (Multiple Electrolytes Injection, Type 1, USP) is compatible with blood or blood components. It may be administered prior to or following the infusion of blood through the same administration set (i.e., as a priming solution), added to or infused concurrently with blood components, or used as a diluent in the transfusion of packed erythrocytes. PLASMA-LYTE A Injection and 0.9% Sodium Chloride Injection, USP are equally compatible with blood or blood components.

CONTRAINDICATIONS

None known

WARNINGS

PLASMA-LYTE A Injection pH 7.4 (Multiple Electrolytes Injection, Type 1, USP) should be used with great care, if at all, in patients with congestive heart failure, severe renal insufficiency, and in clinical states in which there exists edema with sodium retention.
PLASMA-LYTE A Injection pH 7.4 (Multiple Electrolytes Injection, Type 1, USP) should be used with great care, if at all, in patients with hyperkalemia, severe renal failure, and in conditions in which potassium retention is present.
PLASMA-LYTE A Injection pH 7.4 (Multiple Electrolytes Injection, Type 1, USP) should be used with great care in patients with metabolic or respiratory alkalosis. The administration of acetate or gluconate ions should be done with great care in those conditions in which there is an increased level or an impaired utilization of these ions, such as severe hepatic insufficiency.
The intravenous administration of PLASMA-LYTE A Injection pH 7.4 (Multiple Electrolytes Injection, Type 1, USP) can cause fluid and/or solute overloading resulting in dilution of serum electrolyte concentrations, overhydration, congested states, or pulmonary edema. The risk of dilutional states is inversely proportional to the electrolyte concentrations of the injection. The risk of solute overload causing congested states with peripheral and pulmonary edema is directly proportional to the electrolyte concentrations of the injection.
In patients with diminished renal function, administration of PLASMA-LYTE A Injection pH 7.4 (Multiple Electrolytes Injection, Type 1, USP) may result in sodium or potassium retention.

ADVERSE REACTIONS

Reactions which may occur because of the solution or the technique of administration include febrile response, infection at the site of injection, venous thrombosis or phlebitis extending from the site of injection, extravasation, and hypervolemia. If an adverse reaction does occur, discontinue the infusion, evaluate the patient, institute appropriate therapeutic countermeasures, and save the remainder of the fluid for examination if deemed necessary.

PRECAUTIONS

Clinical evaluation and periodic laboratory determinations are necessary to monitor changes in fluid balance, electrolyte concentrations, and acid base balance during prolonged parenteral therapy or whenever the condition of the patient warrants such evaluation.
PLASMA-LYTE A Injection pH 7.4 (Multiple Electrolytes Injection, Type 1, USP) should be used with caution. Excess administration may result in metabolic alkalosis.
Caution must be exercised in the administration of PLASMA-LYTE A Injection pH 7.4 (Multiple Electrolytes Injection, Type 1, USP) to patients receiving corticosteroids or corticotropin.
Do not administer unless solution is clear and seal is intact.

DOSAGE AND ADMINISTRATION

As directed by a veterinarian. Dosage is dependent upon the age, weight and clinical condition of the patient as well as laboratory determinations.
Parenteral drug products should be inspected visually for particulate matter and discoloration prior to administration whenever solution and container permit.
All injections in plastic containers are intended for intravenous administration using sterile equipment.
Additives may be incompatible. Complete information is not available. Those additives known to be incompatible should not be used. Consult with pharmacist, if available. If, in the informed judgment of the
veterinarian, it is deemed advisable to introduce additives, use aseptic technique. Mix thoroughly when additives have been introduced. Do not store solutions containing additives.

OVERDOSAGE

In an event of overhydration or solute overload, re-evaluate the patient and institute appropriate corrective measures. See Warnings, Precautions and Adverse Events.

HOW SUPPLIED

PLASMA-LYTE A Injection pH 7.4 (Multiple Electrolytes Injection, Type 1, USP) in plastic container is available as shown below:

Size
(mL) | Code | NDC
5000 | 2B8229 | NDC 0338-0090-02

Exposure of pharmaceutical products to heat should be minimized. Avoid excessive heat. It is recommended the product be stored at room temperature (25°C/77°F); brief exposure up to 40°C/104°F does not adversely affect the product.

Directions for use of plastic container

To Open
Tear overwrap down side at slit and remove solution container. Visually inspect the container. If the outlet port protector is damaged, detached, or not present, discard container as solution path sterility may be impaired. Some opacity of the plastic due to moisture absorption during the sterilization process may be observed. This is normal and does not affect the solution quality or safety. The opacity will diminish gradually. Check for minute leaks by squeezing inner bag firmly. If leaks are found, discard solution as sterility may be impaired. If supplemental medication is desired, follow directions below.

Preparation for Administration

1. Suspend container from eyelet support.
2. Remove plastic protector from outlet port at bottom of container.
3. Attach administration set. Refer to complete directions accompanying
  set.

Container Label

Veterinary PLASMA-LYTE A
Injection pH 7.4
(Multiple Electrolytes Injection Type 1 USP)

5000 mL

Each 100 mL Contains 526 mg Sodium Chloride
USP 502 mg Sodium Gluconate USP 368 mg Sodium
Acetate Trihydrate USP 37 mg Potassium Chloride
USP 30 mg Magnesium chloride usp pH adjusted
with Sodium Hydroxide pH 7.4 (6.5 to 8.0) mEq/L
Sodium 140 Potassium 5 Magnesium 3 Chloride 98
Acetate 27 Gluconate 23 Osmolarity 294 mOsmol/L
(calc) Sterile Nonpyrogenic SinglGLe dose container
Contains no antimicrobial agents Use solution promptly
Following initial entry Additives may be incompatible
Consult with pharmacist if available When introducing
additives use aseptic technique Mix thoroughly Discard
unused portion Dosage Intravenously as directed by
a veterinarian See package insert Cautions Squeeze
and inspect inner bag which maintains product sterility
Discard if leaks are found Do not use unless solution
is clear and seal is intact Store unit in moisture
barrier overwrap at room temperature (25°C/77°F)
until ready to use Avoid excessive heat

For animal use only
Caution Federal (usa) law restricts this drug to use by
or on the order of a licensed veterinarian

Baxter and Plasma-lyte are trademarks
of Baxter International, Inc.

For customer service call

NDC 0338-0090-02

800 933 0303

2B8229

Baxter Healthcare Corporation
Deerfield, IL 60015 USA

Made in USA

Baxter Logo

4500

4000

3500

3000

2500

2000

1500

1000

500